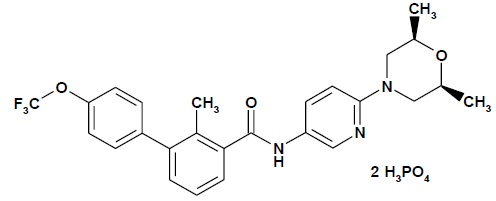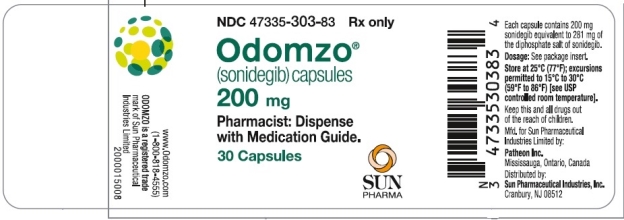 DRUG LABEL: Odomzo
NDC: 47335-303 | Form: CAPSULE
Manufacturer: Sun Pharmaceutical Industries, Inc.
Category: prescription | Type: HUMAN PRESCRIPTION DRUG LABEL
Date: 20241231

ACTIVE INGREDIENTS: SONIDEGIB PHOSPHATE 200 mg/1 1
INACTIVE INGREDIENTS: SILICON DIOXIDE; CROSPOVIDONE; LACTOSE MONOHYDRATE; MAGNESIUM STEARATE; POLOXAMER 188; SODIUM LAURYL SULFATE; GELATIN, UNSPECIFIED; FERRIC OXIDE RED; TITANIUM DIOXIDE; AMMONIA; FERROSOFERRIC OXIDE; PROPYLENE GLYCOL; SHELLAC

HIGHLIGHTS OF PRESCRIBING INFORMATION

These highlights do not include all the information needed to use ODOMZO safely and effectively. See full prescribing information for ODOMZO.
ODOMZO® (sonidegib) capsules, for oral use
Initial U.S. Approval: 2015

WARNING: EMBRYO-FETAL TOXICITY

See full prescribing information for complete boxed warning.

- ODOMZO can cause embryo-fetal death or severe birth defects when administered to a pregnant woman and is embryotoxic, fetotoxic, and teratogenic in animals. (5.1, 8.1)
- Verify the pregnancy status of females of reproductive potential prior to initiating therapy. Advise females of reproductive potential to use effective contraception during treatment with ODOMZO and for at least 20 months after the last dose. (5.1, 8.3)
- Advise males of the potential risk of exposure through semen and to use condoms with a pregnant partner or a female partner of reproductive potential during treatment with ODOMZO and for at least 8 months after the last dose. (5.1, 8.3)

1 INDICATIONS AND USAGE

ODOMZO is a hedgehog pathway inhibitor indicated for the treatment of adult patients with locally advanced basal cell carcinoma (BCC) that has recurred following surgery or radiation therapy, or those who are not candidates for surgery or radiation therapy. (1)

2 DOSAGE AND ADMINISTRATION

Recommended dosage: 200 mg orally once daily taken on an empty stomach, at least 1 hour before or 2 hours after a meal. (2.2)

3 DOSAGE FORMS AND STRENGTHS

200 mg capsules (3)

4 CONTRAINDICATIONS

None. (4)

5 WARNINGS AND PRECAUTIONS

- Embryo-Fetal Toxicity: Advise patients not to donate blood or blood products during treatment with ODOMZO and for at least 20 months after the last dose. (5.1)
- Musculoskeletal Adverse Reactions: Obtain serum creatine kinase (CK) and creatinine levels prior to initiating therapy, periodically during treatment, and as clinically indicated. Temporary dose interruption or discontinuation of ODOMZO may be required based on the severity of musculoskeletal adverse reactions. (2.2, 5.2)
- Premature fusion of the epiphyses (5.3, 8.4)

6 ADVERSE REACTIONS

The most common adverse reactions occurring in ≥10% of patients are muscle spasms, alopecia, dysgeusia, fatigue, nausea, musculoskeletal pain, diarrhea, decreased weight, decreased appetite, myalgia, abdominal pain, headache, pain, vomiting, and pruritus. (6.1)

To report SUSPECTED ADVERSE REACTIONS, contact Sun Pharmaceutical Industries, Inc. at 1-800-406-7984 or FDA at 1-800-FDA-1088 or www.fda.gov/medwatch.

7 DRUG INTERACTIONS

- CYP3A inhibitors: Avoid strong CYP3A inhibitors. Avoid long-term (greater than 14 days) use of moderate CYP3A inhibitors. (7.1)
- CYP3A inducers: Avoid strong and moderate CYP3A inducers. (7.1)

8 USE IN SPECIFIC POPULATIONS

- Lactation: Advise not to breastfeed. (8.2)

FULL PRESCRIBING INFORMATION

WARNING: EMBRYO-FETAL TOXICITY

- ODOMZO can cause embryo-fetal death or severe birth defects when administered to a pregnant woman. ODOMZO is embryotoxic, fetotoxic, and teratogenic in animals [see Warnings and Precautions (5.1) and Use in Specific Populations (8.1)].
- Verify the pregnancy status of females of reproductive potential prior to initiating therapy. Advise females of reproductive potential to use effective contraception during treatment with ODOMZO and for at least 20 months after the last dose [see Warnings and Precautions (5.1) and Use in Specific Populations (8.3)].
- Advise males of the potential risk of exposure through semen and to use condoms with a pregnant partner or a female partner of reproductive potential during treatment with ODOMZO and for at least 8 months after the last dose [see Warnings and Precautions (5.1) and Use in Specific Populations (8.3)].

1 INDICATIONS AND USAGE

ODOMZO (sonidegib) is indicated for the treatment of adult patients with locally advanced basal cell carcinoma (BCC) that has recurred following surgery or radiation therapy, or those who are not candidates for surgery or radiation therapy.

2 DOSAGE AND ADMINISTRATION

2.1 Important Safety Information

Verify the pregnancy status of females of reproductive potential prior to initiating ODOMZO [see Use in Specific Populations (8.1, 8.3)].

2.2 Recommended Dosage

The recommended dosage of ODOMZO is 200 mg taken orally once daily on an empty stomach, at least 1 hour before or 2 hours after a meal, administered until disease progression or unacceptable toxicity [see Clinical Pharmacology (12.3)].

Obtain serum creatine kinase (CK) levels and renal function tests prior to initiating ODOMZO in all patients [see Dosage and Administration (2.2) and Warnings and Precautions (5.2)].

If a dose of ODOMZO is missed, resume dosing with the next scheduled dose.

2.3 Dosage Modifications for Adverse Reactions

Interrupt ODOMZO for

- Severe or intolerable musculoskeletal adverse reactions.
- First occurrence of serum CK elevation between 2.5 and 10 times upper limit of normal (ULN).
- Recurrent serum CK elevation between 2.5 and 5 times ULN.

Resume ODOMZO at 200 mg daily upon resolution of clinical signs and symptoms.

Permanently discontinue ODOMZO for

- Serum CK elevation greater than 2.5 times ULN with worsening renal function.
- Serum CK elevation greater than 10 times ULN.
- Recurrent serum CK elevation greater than 5 times ULN.
- Recurrent severe or intolerable musculoskeletal adverse reactions.

3 DOSAGE FORMS AND STRENGTHS

Capsules: 200 mg, opaque pink colored with ‘SONIDEGIB 200MG’ printed on the body and ‘NVR’ printed on the cap in black ink (equivalent to 281 mg of diphosphate salt of sonidegib).

4 CONTRAINDICATIONS

None.

5 WARNINGS AND PRECAUTIONS

5.1 Embryo-Fetal Toxicity

ODOMZO can cause embryo-fetal death or severe birth defects when administered to a pregnant woman. In animal reproduction studies, sonidegib was embryotoxic, fetotoxic, and teratogenic at maternal exposures below the recommended human dose of 200 mg [see Use in Specific Populations (8.1)].

Females of Reproductive Potential

Verify pregnancy status of females of reproductive potential prior to initiating ODOMZO treatment. Advise pregnant women of the potential risk to a fetus. Advise females to use effective contraception during treatment with ODOMZO and for at least 20 months after the last dose [see Use in Specific Populations (8.3)].

Males

Advise male patients with female partners to use condoms, even after a vasectomy, during treatment with ODOMZO and for at least 8 months after the last dose to avoid potential drug exposure in pregnant females or females of reproductive potential [see Use in Specific Populations (8.3)].

Blood Donation

Advise patients not to donate blood or blood products while taking ODOMZO and for at least 20 months after the last dose of ODOMZO, because their blood or blood products might be given to a female of reproductive potential.

5.2 Musculoskeletal Adverse Reactions

Musculoskeletal adverse reactions, which may be accompanied by serum creatine kinase (CK) elevations, occur with ODOMZO and other drugs which inhibit the hedgehog (Hh) pathway.

In a pooled safety analysis of 12 clinical studies involving 571 patients with various advanced cancers treated with ODOMZO at doses ranging from 100 mg to 3000 mg, rhabdomyolysis (defined as serum CK increase of more than ten times the baseline value with a concurrent 1.5-fold or greater increase in serum creatinine above baseline value) occurred in one patient (0.2%) treated with ODOMZO 800 mg.

In the BOLT study, musculoskeletal adverse reactions occurred in 68% (54/79) of patients treated with ODOMZO 200 mg daily with 9% (7/79) reported as Grade 3 or 4. The most frequent manifestations of musculoskeletal adverse reactions reported as an adverse event were muscle spasms (54%), musculoskeletal pain (32%), and myalgia (19%). Increased serum CK laboratory values occurred in 61% (48/79) of patients with 8% (6/79) of patients having Grade 3 or 4 serum CK elevations. Musculoskeletal pain and myalgia usually preceded serum CK elevation. Among patients with Grade 2 or higher CK elevations, the median time to onset was 12.9 weeks (range: 2 to 39 weeks) and the median time to resolution (to ≤ Grade 1) was 12 days (95% CI: 8 to 14 days). ODOMZO was temporarily interrupted in 8% of patients or permanently discontinued in 8% of patients for musculoskeletal adverse reactions. The incidence of musculoskeletal adverse reactions requiring medical intervention (magnesium supplementation, muscle relaxants, and analgesics or narcotics) was 29%, including four patients (5%) who received intravenous hydration or were hospitalized.

Obtain baseline serum CK and creatinine levels prior to initiating ODOMZO, periodically during treatment, and as clinically indicated (e.g., if muscle symptoms are reported). Obtain serum creatinine and CK levels at least weekly in patients with musculoskeletal adverse reactions with concurrent serum CK elevation greater than 2.5 times ULN until resolution of clinical signs and symptoms. Depending on the severity of symptoms, temporary dose interruption or discontinuation may be required for musculoskeletal adverse reactions or serum CK elevation [see Dosage and Administration (2.2)]. Advise patients starting therapy with ODOMZO of the risk of muscle-related adverse reactions. Advise patients to report promptly any new unexplained muscle pain, tenderness or weakness occurring during treatment or that persists after discontinuing ODOMZO.

5.3 Premature Fusion of the Epiphyses

Premature fusion of the epiphyses has been reported in pediatric patients exposed to ODOMZO and other Hh pathway inhibitors. Despite discontinuation of drug, cases of progressive of epiphyseal fusion have been reported in pediatric patients receiving other Hh pathway inhibitors. ODOMZO is not indicated for use in pediatric patients.

6 ADVERSE REACTIONS

The following clinically significant adverse reactions are described elsewhere in the labeling:

- Musculoskeletal Adverse Reactions [see Warnings and Precautions (5.2)].

6.1 Clinical Trials Experience

Because clinical trials are conducted under widely varying conditions, adverse reaction rates observed in the clinical trials of a drug cannot be directly compared to rates in the clinical trials of another drug and may not reflect the rates observed in clinical practice.

The safety of ODOMZO was evaluated in BOLT, a randomized, double-blind, multiple cohort trial in which 229 patients received ODOMZO at either 200 mg (n=79) or 800 mg (n=150) daily. The frequency of common adverse reactions including muscle spasms, alopecia, dysgeusia, fatigue, nausea, decreased weight, decreased appetite, myalgia, pain, and vomiting was greater in patients treated with ODOMZO 800 mg as compared to 200 mg.

The data described below reflect exposure to ODOMZO 200 mg daily in 79 patients with locally advanced BCC (laBCC; n=66) or metastatic BCC (mBCC; n=13) enrolled in BOLT. Patients were followed for at least 18 months unless discontinued earlier. The median duration of treatment with ODOMZO was 11.0 months (range 1.3 to 33.5 months).

The study population characteristics were: median age of 67 years (range 25 to 92; 59% were ≥65 years), 61% male, and 90% white. The majority of patients had prior surgery (75%), radiotherapy (24%), systemic chemotherapy (4%), or topical or photodynamic therapies (18%) for treatment of BCC. No patient had prior exposure to a Hh pathway inhibitor.

ODOMZO was permanently discontinued in 34% of patients or temporarily interrupted in 20% of patients for adverse reactions. Adverse reactions reported in at least two patients that led to discontinuation of the drug were: muscle spasms, and dysgeusia (each 5%), asthenia, increased lipase, and nausea (each 4%), fatigue, decreased appetite, alopecia, and decreased weight (each 3%). Serious adverse reactions occurred in 18% of patients.

The most common adverse reactions occurring in ≥10% of patients treated with ODOMZO 200 mg were muscle spasms, alopecia, dysgeusia, fatigue, nausea, musculoskeletal pain, diarrhea, decreased weight, decreased appetite, myalgia, abdominal pain, headache, pain, vomiting, and pruritus (Table 1).

The key laboratory abnormalities are described in Table 2.

Table 1: Adverse Reactions Occurring in ≥10% of Patients in BOLT

Adverse Reaction | ODOMZO 200 mg (N=79)
 | All Gradesa % | Grade 3 %
Musculoskeletal and connective tissue
Muscle spasms | 54 | 3
Musculoskeletal pain | 32 | 1
Myalgia | 19 | 0
Skin and subcutaneous tissue
Alopecia | 53 | 0
Pruritus | 10 | 0
Nervous system
Dysgeusia | 46 | 0
Headache | 15 | 1
General
Fatigue | 41 | 4
Pain | 14 | 1
Gastrointestinal
Nausea | 39 | 1
Diarrhea | 32 | 1
Abdominal pain | 18 | 0
Vomiting | 11 | 1
Investigations
Decreased weight | 30 | 3
Metabolism and nutrition
Decreased appetite | 23 | 1
a No Grade 4 adverse reactions were reported.

Table 2: Key Laboratory Abnormalitiesa in BOLT

Laboratory Test | ODOMZO 200 mg (N=79)
 | All Grades % | Grades 3-4 %
Chemistry
Increased serum creatinine | 92b | 0
Increased serum creatine kinase (CK) | 61 | 8
Hyperglycemia | 51 | 4
Increased lipase | 43 | 13
Increased alanine aminotransferase | 19 | 4
Increased aspartate aminotransferase | 19 | 4
Increased amylase | 16 | 1
Hematology
Anemia | 32 | 0
Lymphopenia | 28 | 3
a Based on worst post-treatment laboratory value regardless of baseline; grading by CTCAE v4.03.
b The serum creatinine level remained within normal range in 76% (60/79) of patients.

Amenorrhea

Amenorrhea lasting for at least 18 months occurred in two of 14 pre-menopausal women treated with ODOMZO 200 mg or 800 mg once daily.

7 DRUG INTERACTIONS

7.1 Effects of Other Drugs on ODOMZO

Strong and Moderate CYP3A Inhibitors

Avoid concomitant administration of ODOMZO with strong CYP3A inhibitors [see Clinical Pharmacology (12.3)].

Avoid concomitant administration of ODOMZO with moderate CYP3A inhibitors. If a moderate CYP3A inhibitor must be used, administer the moderate CYP3A inhibitor for less than 14 days and monitor closely for adverse reactions particularly musculoskeletal adverse reactions [see Clinical Pharmacology (12.3)].

Strong and Moderate CYP3A Inducers

Avoid concomitant administration of ODOMZO with strong and moderate CYP3A inducers [see Clinical Pharmacology (12.3)].

8 USE IN SPECIFIC POPULATIONS

8.1 Pregnancy

Risk Summary

Based on its mechanism of action and data from animal reproduction studies, ODOMZO can cause fetal harm when administered to a pregnant woman [see Clinical Pharmacology (12.1)]. There are no available data on the use of ODOMZO in pregnant women. In animal reproduction studies, oral administration of sonidegib during organogenesis at doses below the recommended human dose of 200 mg resulted in embryotoxicity, fetotoxicity, and teratogenicity in rabbits (see Data). Teratogenic effects observed included severe midline defects, missing digits, and other irreversible malformations. Advise pregnant women of the potential risk to a fetus. Report pregnancies to Sun Pharmaceutical Industries, Inc. at 1-800-406-7984.

In the U.S. general population, the estimated background risk of major birth defects is 2-4% and of miscarriage in clinically recognized pregnancies is 15-20%.

Data

Animal Data

Daily oral administration of sonidegib to pregnant rabbits resulted in abortion, complete resorption of fetuses, or severe malformations at ≥ 5 mg/kg/day (approximately 0.05 times the recommended human dose based on AUC). Teratogenic effects included vertebral, distal limb and digit malformations, severe craniofacial malformations, and other severe midline defects. Skeletal variations were observed when maternal exposure to sonidegib was below the limit of detection.

8.2 Lactation

No data are available regarding the presence of sonidegib in human milk, the effects of the drug on the breastfed infant, or the effects of the drug on milk production. Because of the potential for serious adverse reactions in breastfed infants, advise women not to breastfeed during treatment with ODOMZO and for 20 months after the last dose.

8.3 Females and Males of Reproductive Potential

Based on its mechanism of action and animal data, ODOMZO can cause fetal harm when administered to a pregnant woman [see Use in Specific Populations (8.1)].

Pregnancy Testing

Verify the pregnancy status of females of reproductive potential prior to initiating ODOMZO treatment.

Contraception

Females

Advise females of reproductive potential to use effective contraception during treatment with ODOMZO and for at least 20 months after the last dose.

Males

It is not known if sonidegib is present in semen. Advise male patients to use condoms, even after a vasectomy, to avoid potential drug exposure to pregnant partners and female partners of reproductive potential during treatment with ODOMZO and for at least 8 months after the last dose.

Advise males not to donate semen during treatment with ODOMZO and for at least 8 months after the last dose.

Infertility

Based on findings from animal studies, female fertility may be compromised with ODOMZO [see Nonclinical Toxicology (13.1)].

8.4 Pediatric Use

The safety and effectiveness of ODOMZO have not been established in pediatric patients.

Epiphyseal disorders, including premature fusion of the epiphyses, have been reported in pediatric patients exposed to ODOMZO in a clinical trial. In some cases, pediatric patients treated with other Hh pathway inhibitors have experienced progression of epiphyseal fusion despite discontinuation of the Hh pathway inhibitor.

Juvenile Animal Data

In a 5-week juvenile rat toxicology study, effects of sonidegib were observed in bone, teeth, reproductive tissues, and nerves at doses ≥10 mg/kg/day (approximately 1.2 times the recommended human dose based on AUC). Bone findings included thinning/closure of bone growth plate, decreased bone length and width, and hyperostosis. Findings in teeth included missing or fractured teeth, and atrophy. Reproductive tissue toxicity was evidenced by atrophy of testes, ovaries, and uterus, partial development of the prostate gland and seminal vesicles, and inflammation and aspermia of the epididymis. Nerve degeneration was also noted.

8.5 Geriatric Use

Of the 229 patients who received ODOMZO (79 patients receiving 200 mg daily and 150 patients receiving 800 mg daily) in BOLT, 54% were 65 years and older, while 28% were 75 years and older. No overall differences in effectiveness were observed between these patients and younger patients. There was a higher incidence of serious adverse reactions, Grade 3 and 4 adverse reactions, and adverse reactions requiring dose interruption or discontinuation in patients ≥65 years compared with younger patients; this was not attributable to an increase in any specific adverse event.

11 DESCRIPTION

Sonidegib is a Hh pathway inhibitor. The molecular formula for sonidegib phosphate is C26H26 F3N3O3• 2H3PO4. The molecular weight is 681.49 daltons. The chemical name is N-[6-(cis-2,6-dimethylmorpholin-4-yl)pyridine-3-yl]-2-methyl-4’-(trifluoromethoxy) [1,1’-biphenyl]-3-carboxamide diphosphate. The molecular structure is shown below:

Sonidegib phosphate is a white to off-white powder. Sonidegib freebase is practically insoluble.

ODOMZO (sonidegib) capsules for oral use contain 200 mg of sonidegib as the freebase (equivalent to 281 mg of diphosphate salt of sonidegib) and the following inactive ingredients: colloidal silicon dioxide, crospovidone, lactose monohydrate, magnesium stearate, poloxamer and sodium lauryl sulfate. The opaque pink hard gelatin capsule shell contains gelatin, red iron oxide, and titanium dioxide. The black printing ink contains ammonium hydroxide, black iron oxide, propylene glycol, and shellac.

12 CLINICAL PHARMACOLOGY

12.1 Mechanism of Action

Sonidegib is an inhibitor of the Hh pathway. Sonidegib binds to and inhibits Smoothened, a transmembrane protein involved in Hh signal transduction.

12.2 Pharmacodynamics

Cardiac Electrophysiology

At a dose of 800 mg once daily, sonidegib does not prolong the QTc interval.

12.3 Pharmacokinetics

Sonidegib exhibited dose-proportional increases in the area under the curve (AUC) and the maximal concentration (Cmax) over the dose range of 100 mg to 400 mg, but less than dose-proportional increases at doses greater than 400 mg. Steady-state was reached approximately 4 months after starting ODOMZO and the estimated accumulation at steady-state was 19-fold. Following a dose of 200 mg once daily, the estimated mean steady-state Cmax is 1030 ng/mL, AUC0-24h is 22 μg*h/mL and minimal concentration (Cmin) is 890 ng/mL.

Absorption

Less than 10% of an oral dose of ODOMZO is absorbed. Following the administration of a single ODOMZO dose (100 mg to 3000 mg) under fasted conditions in patients with cancer, the median time-to-peak concentration (Tmax) was 2 to 4 hours.

Effect of Food

A high-fat meal (approximately 1000 calories with 50% of calories from fat) increased exposure to sonidegib (geometric mean AUCinf and Cmax) by 7.4- to 7.8-fold [see Dosage and Administration (2.1)].

Distribution

The estimated apparent steady-state volume of distribution (Vss/F) was 9,166 L. Sonidegib was greater than 97% bound to human plasma proteins in vitro and the binding was concentration independent. In vitro studies suggested that sonidegib is not a substrate of P-glycoprotein, MRP2 or BCRP.

Elimination

The elimination half-life (t1/2) of sonidegib estimated from population pharmacokinetic (PK) modeling was approximately 28 days.

Metabolism

Sonidegib is primarily metabolized by CYP3A. The main circulating compound was unchanged sonidegib (36% of circulating radioactivity).

Excretion

Sonidegib and its metabolites are eliminated primarily by the hepatic route. Of the absorbed dose, approximately 70% was eliminated in the feces and 30% was eliminated in the urine. Unchanged sonidegib was not detectable in the urine.

Specific Populations

Age, body weight, hepatic impairment (Child-Pugh A, B and C), mild to moderate renal impairment (creatinine clearance 30 to 89 mL/min) and sex had no clinically meaningful effect on sonidegib steady-state exposure.

Racial or Ethnic Groups

A cross study comparison suggests that geometric mean AUCinf of sonidegib is 1.7-fold higher in Japanese healthy subjects compared to Western healthy subjects (Whites and Blacks) following a single 200 mg dose of ODOMZO.

Drug Interaction Studies

Effects of CYP3A Inhibitors on Sonidegib

Strong CYP3A inhibitor: The geometric mean sonidegib AUC0-10d increased by 2.2-fold and the Cmax increased by 1.5-fold when ODOMZO at a dose of 800 mg was taken with ketoconazole compared to ODOMZO alone [see Drug Interactions (7.1)]. The geometric mean sonidegib steady-state AUC0-24h would similarly increase in cancer patients taking ODOMZO 200 mg once daily when coadministered with a strong CYP3A inhibitor for 14 days.

Moderate CYP3A inhibitor: The geometric mean sonidegib steady-state AUC0-24h would increase 1.8-fold when ODOMZO 200 mg once daily is coadministered with a moderate CYP3A inhibitor (erythromycin) for 14 days and would increase 2.8-fold when ODOMZO 200 mg once daily is coadministered with a moderate CYP3A inhibitor (erythromycin) for 4 months.

Effects of CYP3A Inducers on Sonidegib

Strong CYP3A inducer: The geometric mean sonidegib AUC0-10d decreased by 72% and the Cmax decreased by 54% when ODOMZO at a dose of 800 mg was taken with rifampicin compared to ODOMZO alone [see Drug Interactions (7.1)].

Moderate CYP3A inducer: The geometric mean sonidegib steady-state AUC0-24h would decrease 56% in cancer patients taking ODOMZO 200 mg once daily when coadministered with a moderate CYP3A inducer (efavirenz) for 14 days and would decrease 69% when coadministered with a moderate CYP3A inducer (efavirenz) for 4 months [see Drug Interactions (7.1)].

Effect of Sonidegib on Cytochrome P450 Enzymes and Transporters

In vitro studies suggested that sonidegib inhibits CYP2B6 and CYP2C9 and it does not induce CYP1A2, CYP2B6 or CYP3A expression or activity.

In vitro studies suggested that sonidegib inhibits BCRP, but not P-glycoprotein, MRP2, OATP1B1, OATP1B3, OAT1, OAT3, OCT1 or OCT2.

Effects of Acid Reducing Agents on Sonidegib

No clinically meaningful effect on sonidegib exposure was observed when ODOMZO at dose of 200 mg was coadministered with esomeprazole, a proton pump inhibitor.

13 NONCLINICAL TOXICOLOGY

13.1 Carcinogenesis, Mutagenesis, Impairment of Fertility

Carcinogenicity studies were performed in mice and rats. No carcinogenic potential was identified in either species.

Sonidegib was not mutagenic in the in vitro bacterial reverse mutation (Ames) assay and was not clastogenic or aneugenic in the in vitro human chromosome aberration assay or in vivo rat bone marrow micronucleus assay.

Sonidegib resulted in a lack of fertility when administered to female rats at ≥20 mg/kg/day (approximately 1.3 times the recommended human dose based on body surface area (BSA). A reduction of the number of pregnant females, an increase in the number of early resorptions, and a decrease in the number of viable fetuses was also noted at 2 mg/kg/day (approximately 0.12 times the recommended human dose based on BSA). In addition, in a 6 month repeat-dose toxicology study in rats, effects on female reproductive organs included atrophy of the uterus and ovaries at doses of 10 mg/kg (approximately ≥2 times the exposure in humans at the recommended dose of 200 mg based on AUC). No adverse effects on fertility were noted when male rats were administered sonidegib at doses up to 20 mg/kg/day, the highest dose tested.

13.2 Animal Toxicology and/or Pharmacology

Body tremors along with significant increases in creatine kinase were observed in rats administered oral sonidegib for 13 weeks or longer at ≥10 mg/kg/day (approximately ≥2 times the recommended human dose based on AUC).

14 CLINICAL STUDIES

The safety and effectiveness of ODOMZO were evaluated in a single, multicenter, double-blind, multiple cohort clinical trial conducted in patients with locally advanced basal cell carcinoma (laBCC) (n=194) or metastatic basal cell carcinoma (mBCC) (n=36) (BOLT, NCT01327053). Patients were randomized (2:1) to receive either ODOMZO 800 mg or 200 mg orally, once daily, until disease progression or intolerable toxicity. Randomization was stratified by stage of disease (locally advanced or metastatic), laBCC disease histology (aggressive vs. non-aggressive), and geographic region. Patients with laBCC were required to have lesions for which radiotherapy was contraindicated or inappropriate (e.g., Gorlin syndrome or limitations because of location of tumor), that had recurred after radiotherapy, that were unresectable or for which surgical resection would result in substantial deformity, or that had recurred after prior surgical resection.

The major efficacy outcome measure of the trial was objective response rate (ORR) as determined by blinded central review according to modified Response Evaluation Criteria in Solid Tumors (mRECIST) for patients with laBCC or RECIST version 1.1 for patients with mBCC. Duration of response (DoR), determined by blinded central review, was a key secondary outcome measure.

For patients with laBCC, the evaluation of tumor response was based on a composite assessment that integrated tumor measurements obtained by radiographic assessments of target lesions (per RECIST 1.1), digital clinical photography, and histopathology assessments (via punch biopsies). All modalities used must have demonstrated absence of tumor to achieve a composite assessment of complete response (CR). Response by digital clinical photography was evaluated by World Health Organization (WHO) adapted criteria [partial response (PR): ≥50% decrease in the sum of the product of perpendicular diameters (SPD) of the lesions, CR: disappearance of all lesions, progressive disease (PD): ≥25% increase in the SPD of the lesions]. Multiple punch biopsies of target lesions were performed to confirm a CR or when a response assessment was confounded by presence of lesion ulceration, cyst, and or scarring/fibrosis.

A total of 66 patients randomized to ODOMZO 200 mg daily had laBCC. Three of these patients had a diagnosis of Gorlin Syndrome. The demographic characteristics of the 66 patients with laBCC were: median age of 67 years (range: 25 to 92 years; 58% were ≥65 years); 58% male, 89% white, and ECOG performance status of 0 (67%). Seventy-six percent of patients had prior therapy for treatment of BCC; this included surgery (73%), radiotherapy (18%), and topical/photodynamic therapies (21%). Approximately half of these patients (56%) had aggressive histology.

Patients with laBCC randomized to receive ODOMZO 200 mg daily were followed for at least 30 months unless discontinued earlier. The ORR was 56% (95% confidence interval: 43, 68), consisting of 3 (5%) complete responses and 34 (52%) partial responses. A pre-specified sensitivity analysis using an alternative definition for complete response, defined as at least a PR according to MRI and/or photography and no evidence of tumor on biopsy of the residual lesion, yielded a CR rate of 21%. The median duration of response was 26.1 months (95% CI:10.1, not reached).

A total of 128 patients randomized to ODOMZO 800 mg daily had laBCC. Twelve of these patients had a diagnosis of Gorlin Syndrome. There was no evidence of better antitumor activity (ORR) among patients with laBCC randomized to receive ODOMZO 800 mg daily and followed for at least 30 months unless discontinued earlier.

16 HOW SUPPLIED/STORAGE AND HANDLING

Each ODOMZO capsule has an opaque pink color with ‘SONIDEGIB 200MG’ printed on the capsule body and ‘NVR’ printed on the cap in black ink. ODOMZO capsules are supplied as follows:

Bottle of 30 capsules NDC 47335-303-83

Store at 25°C (77°F); excursions permitted to 15°C to 30°C (59°F to 86°F) [see USP Controlled Room Temperature].

17 PATIENT COUNSELING INFORMATION

Advise the patient to read the FDA-approved patient labeling (Medication Guide).

Embryo-Fetal Toxicity [see Warnings and Precautions (5.1) and Use in Specific Populations (8.1, 8.3)].

Females of Reproductive Potential

- Advise female patients of the potential risk to a fetus. Advise female patients and female partners of male patients to contact their healthcare provider with a known or suspected pregnancy.
- Advise females of reproductive potential to use effective contraception during treatment with ODOMZO and for at least 20 months after the last dose.
- Advise females who may have been exposed to ODOMZO during pregnancy, either directly or through seminal fluid, to contact Sun Pharmaceutical Industries Inc. at 1-800-406-7984.

Males

- Advise males, even those with prior vasectomy, to use condoms, to avoid potential drug exposure in both pregnant partners and female partners of reproductive potential during treatment with ODOMZO and for at least 8 months after the last dose.

Blood Donation

- Advise patients not to donate blood or blood products while taking ODOMZO and for 20 months after stopping treatment.

Musculoskeletal Adverse Reactions

Advise patients to contact their healthcare provider immediately for new or worsening signs or symptoms of muscle toxicity, dark urine, decreased urine output, or the inability to urinate [see Warnings and Precautions (5.2)].

Administration Instructions

Advise patients to take ODOMZO on an empty stomach, at least 1 hour before or 2 hours after a meal [see Dosage and Administration (2.1)].

Lactation

Advise women not to breastfeed during treatment with ODOMZO and for up to 20 months after the last dose [see Use in Specific Populations (8.2)].

Manufactured for Sun Pharmaceutical Industries Limited.

By:

Patheon Inc.
Mississauga, Ontario L5N 7K9, Canada

Distributed by:

Sun Pharmaceutical Industries, Inc.
Cranbury, NJ 08512

ODOMZO is a registered trademark of Sun Pharmaceutical Industries Limited.

© 2022 Sun Pharmaceutical Industries, Inc.

All rights reserved.

Rev. 08/2023

2000016519 US

MEDICATION GUIDE
ODOMZO® (o-DOM-zo)
(sonidegib)
capsules

What is the most important information I should know about ODOMZO?

ODOMZO can cause your baby to die before it is born (be stillborn) or cause your baby to have severe birth defects.

For females who can become pregnant:

- You should talk to your healthcare provider about the risks of ODOMZO to your unborn child.
- Your healthcare provider will do a pregnancy test before you start taking ODOMZO.
- In order to avoid pregnancy, you should use birth control during treatment, and for at least 20 months after your final dose of ODOMZO. Talk to your healthcare provider about what birth control method is right for you during this time.
- Talk to your healthcare provider right away if you have unprotected sex or if you think your birth control has failed.
- Tell your healthcare provider right away if you become pregnant or think that you may be pregnant.

For males:

- It is not known if ODOMZO is present in semen. Do not donate semen while you are taking ODOMZO and for at least 8 months after your final dose.
- You should always use a condom, even if you have had a vasectomy, during sex with female partners who are pregnant or who are able to become pregnant, during treatment with ODOMZO and for at least 8 months after your final dose to protect your female partner from being exposed to ODOMZO.
- Tell your healthcare provider right away if your partner becomes pregnant or thinks she is pregnant while you are taking ODOMZO.

Exposure to ODOMZO during pregnancy:
If you think that you or your female partner may have been exposed to ODOMZO during pregnancy, talk to your healthcare provider right away. If you become pregnant during treatment with ODOMZO, you or your healthcare provider should report your pregnancy to Sun Pharmaceutical Industries, Inc. at 1-800-406-7984.

What is ODOMZO?

ODOMZO is a prescription medicine used to treat adults with a type of skin cancer, called basal cell carcinoma, that has come back following surgery or radiation or that cannot be treated with surgery or radiation.

It is not known if ODOMZO is safe and effective in children.

What should I tell my healthcare provider before taking ODOMZO?

Before you take ODOMZO, tell your healthcare provider if you:

- have muscle pain or spasms, or have a history of a muscle disorder called rhabdomyolysis or myopathy
- have any other medical conditions
- are pregnant or plan to become pregnant. See “What is the most important information I should know about ODOMZO?”
- are breastfeeding or plan to breastfeed. It is not known if ODOMZO passes into your breast milk. Do not breastfeed during treatment and for 20 months after your final dose of ODOMZO. Talk to your healthcare provider about the best way to feed your baby during this time.

Tell your healthcare provider about all the medicines you take, including prescription and over-the-counter medicines, vitamins, and herbal supplements.

How should I take ODOMZO?

- Take ODOMZO exactly as your healthcare provider tells you.
- Take ODOMZO 1 time each day.
- Take ODOMZO at least 1 hour before or 2 hours after a meal.
- If you miss a dose, skip the missed dose. Take your next dose as scheduled.

What should I avoid while taking ODOMZO?

- Do not donate blood or blood products while you are taking ODOMZO and for 20 months after your final dose.
- Do not donate semen while taking ODOMZO and for at least 8 months after your final dose.

What are possible side effects of ODOMZO?

ODOMZO can cause serious side effects, including:

- See “What is the most important information I should know about ODOMZO?”
- Muscle Problems. Muscle spasms and muscle pain are common with ODOMZO, but can also sometimes be symptoms of serious muscle problems. ODOMZO can increase your risk of muscle pain and, rarely a serious condition caused by injury to the muscles (rhabdomyolysis) that can lead to kidney damage. Tell your healthcare provider right away if you develop any new or worsening muscle spasms, pain or tenderness, dark urine, or decreased amount of urine during treatment with ODOMZO.
  Your healthcare provider should do a blood test to check for muscle problems and to check your kidney function before you start taking ODOMZO, during treatment, and if you develop muscle problems.

The most common side effects of ODOMZO include:

- hair loss

- change in taste

- tiredness

- nausea

- diarrhea

- weight loss

- decreased appetite

- stomach area (abdominal) pain

- headache

- vomiting

- itching

ODOMZO can cause absence of menstrual periods (amenorrhea) in females who are able to become pregnant. It is not known if amenorrhea is permanent. Talk to your healthcare provider if you have concerns about fertility.

These are not all of the possible side effects of ODOMZO.

Call your doctor for medical advice about side effects. You may report side effects to FDA at 1-800-FDA-1088.

How should I store ODOMZO?

- Store ODOMZO at room temperature between 68°F to 77°F (20°C to 25°C).

Keep ODOMZO and all medicines out of the reach of children.

General information about the safe and effective use of ODOMZO

Medicines are sometimes prescribed for purposes other than those listed in a Medication Guide. Do not use ODOMZO for a condition for which it was not prescribed. Do not give ODOMZO to other people, even if they have the same symptoms that you have. It may harm them. You can ask your pharmacist or healthcare provider for information about ODOMZO that is written for health professionals.

What are the ingredients in ODOMZO?

Active ingredient: sonidegib

Inactive ingredients: colloidal silicon dioxide, crospovidone, lactose monohydrate, magnesium stearate, poloxamer, and sodium lauryl sulfate. The capsule shell contains gelatin, red iron oxide, and titanium dioxide. The black printing ink contains ammonium hydroxide, black iron oxide, propylene glycol, and shellac.

Manufactured for Sun Pharmaceutical Industries Limited by: Patheon Inc., Mississauga, Ontario L5N 7K9, Canada.

Distributed by: Sun Pharmaceutical Industries, Inc., Cranbury, NJ 08512. For more information, go to www.odomzo.com or call 1-800-818-4555.

ODOMZO is a registered trademark of Sun Pharmaceutical Industries Limited

This Medication Guide has been approved by the U.S. Food and Drug Administration.

2000016519 US Revised 08/2023

PRINCIPAL DISPLAY PANEL

NDC 47335-303-83 Rx only

Odomzo®

(sonidegib) capsules

200 mg

Pharmacist: Dispense with Medication Guide.

30 Capsules

SUN PHARMA